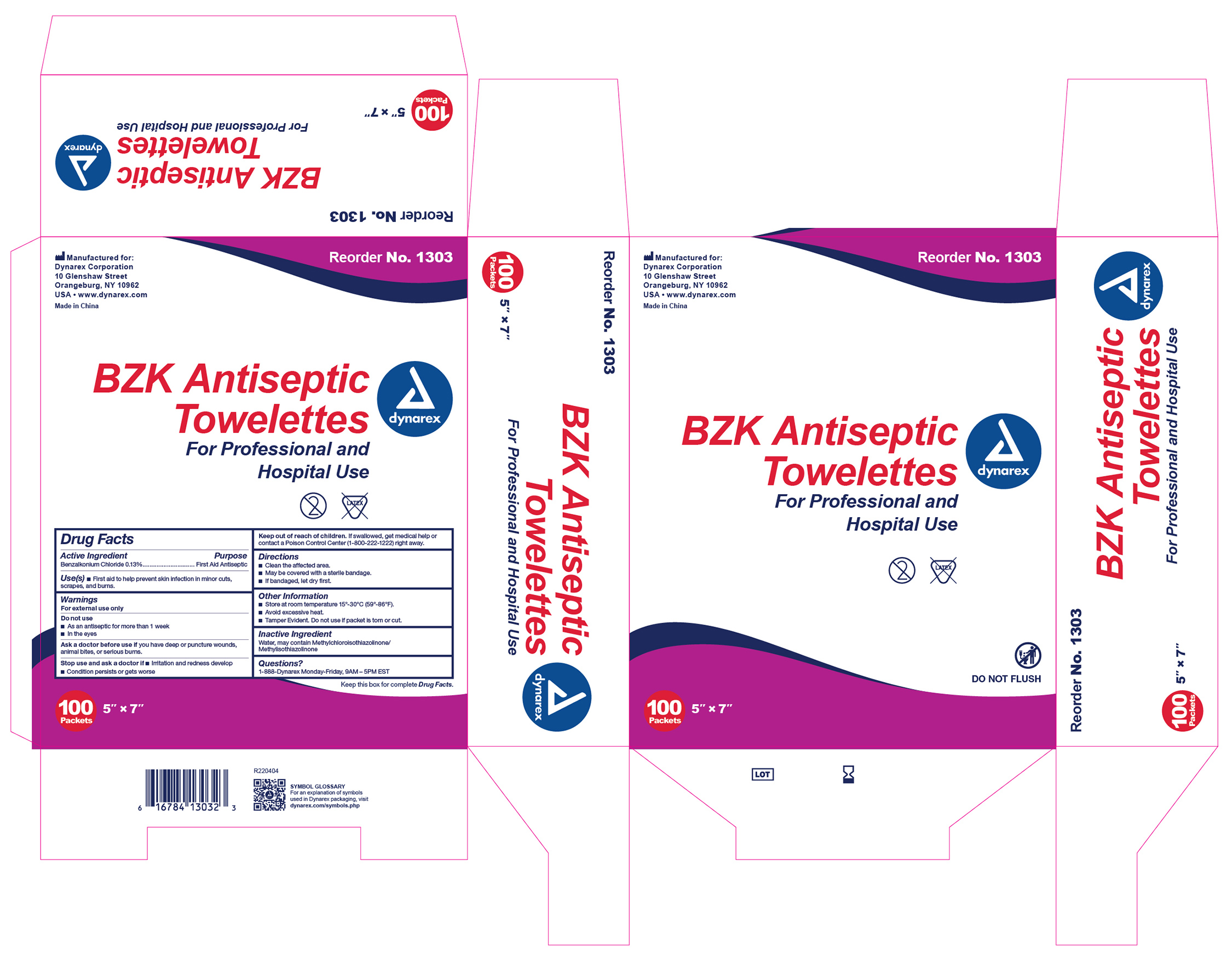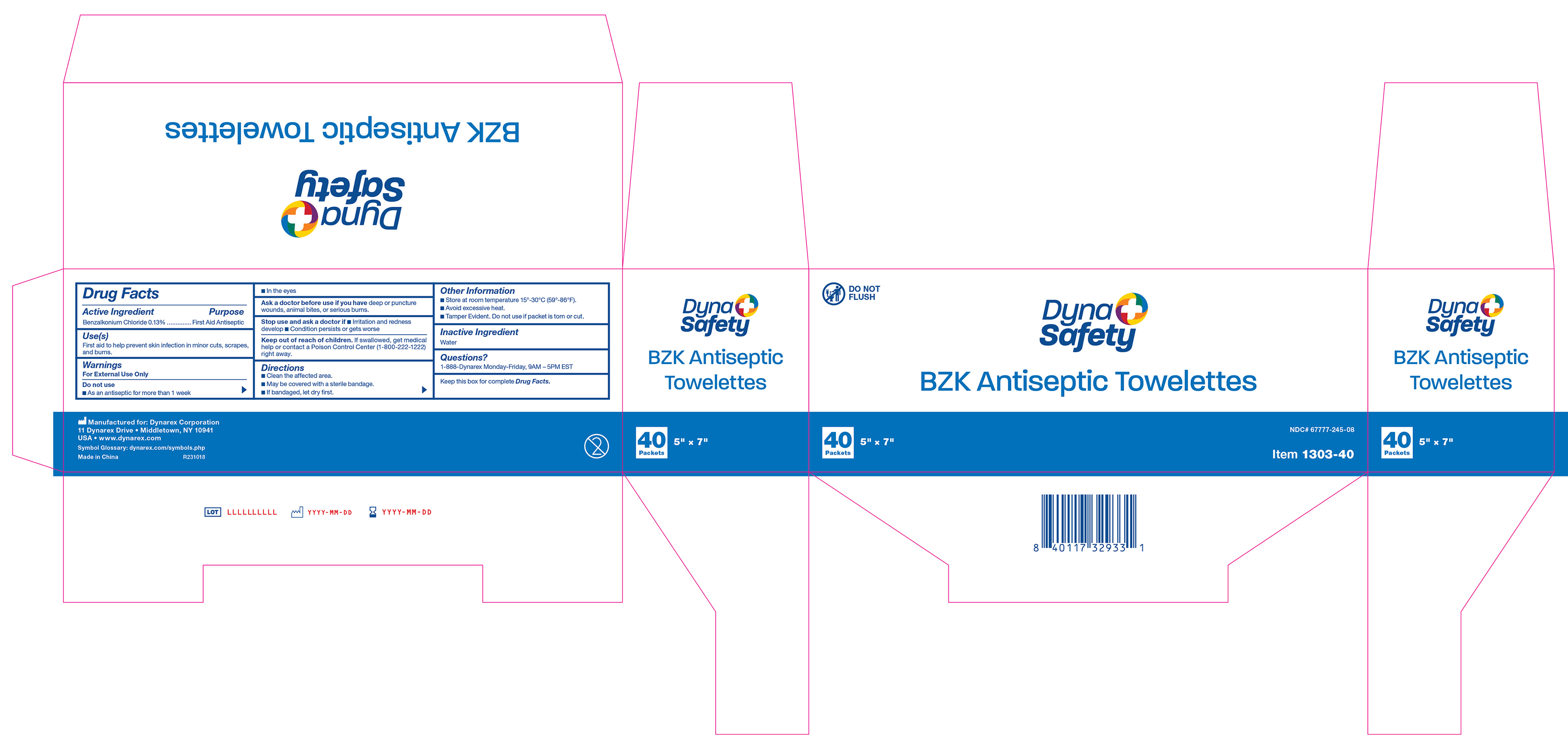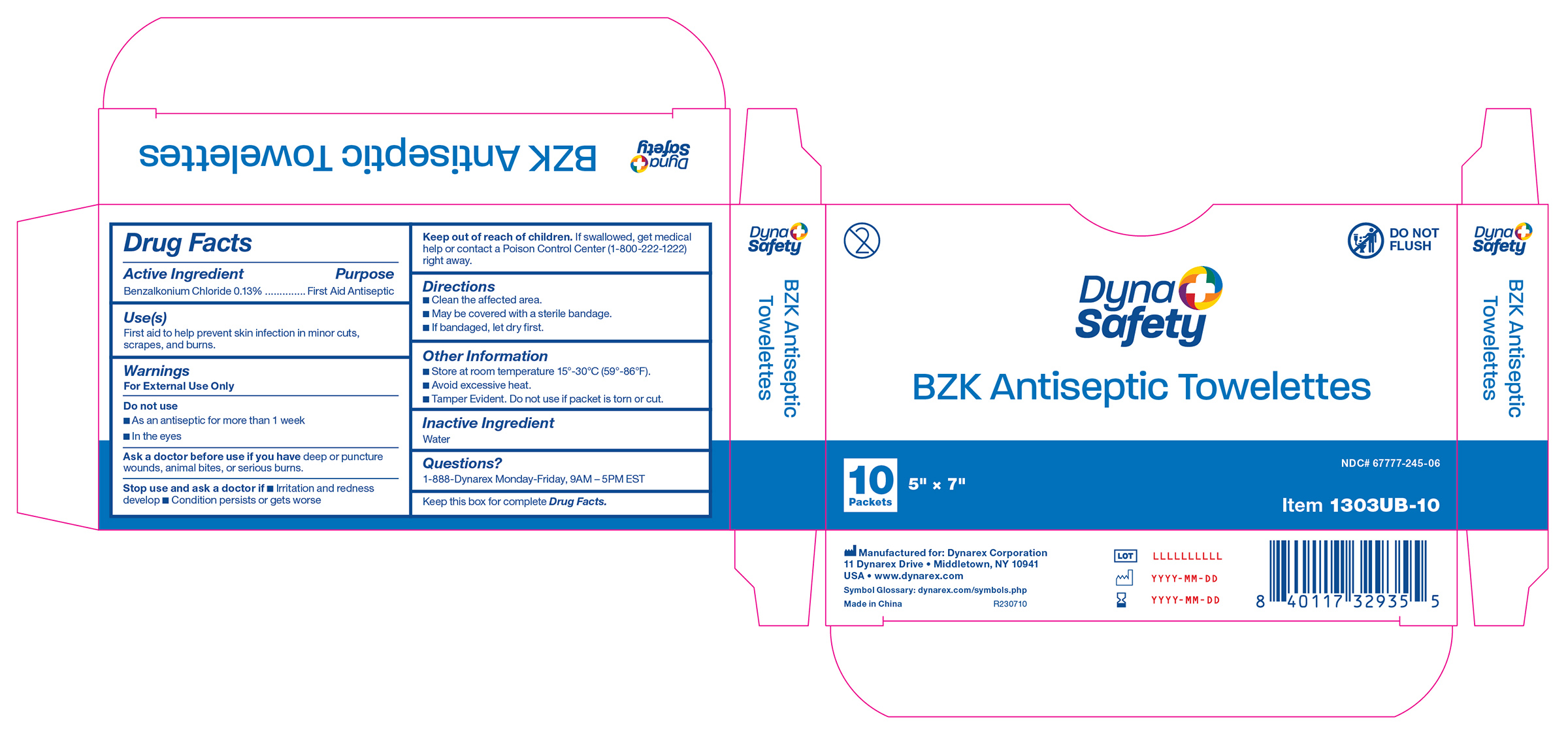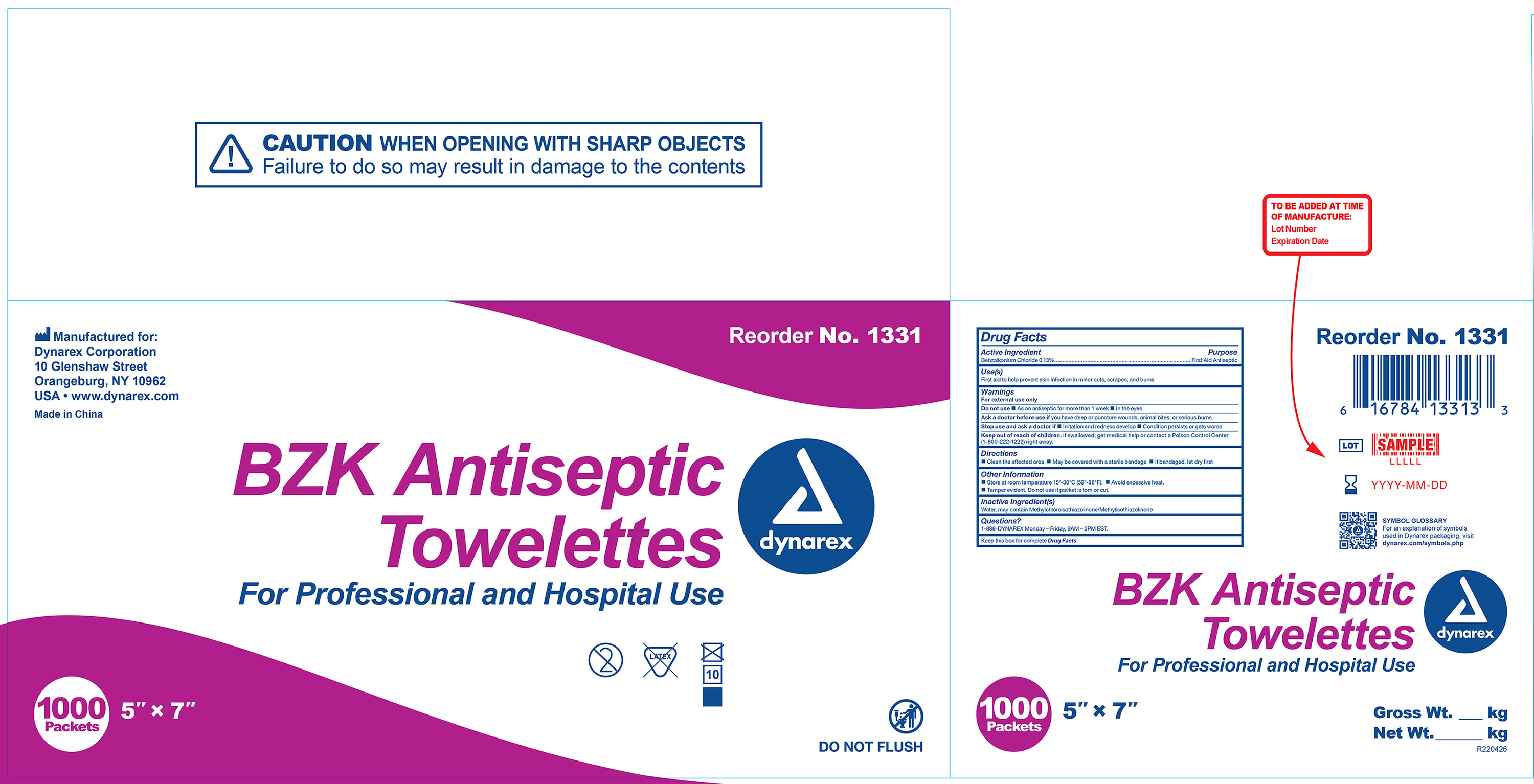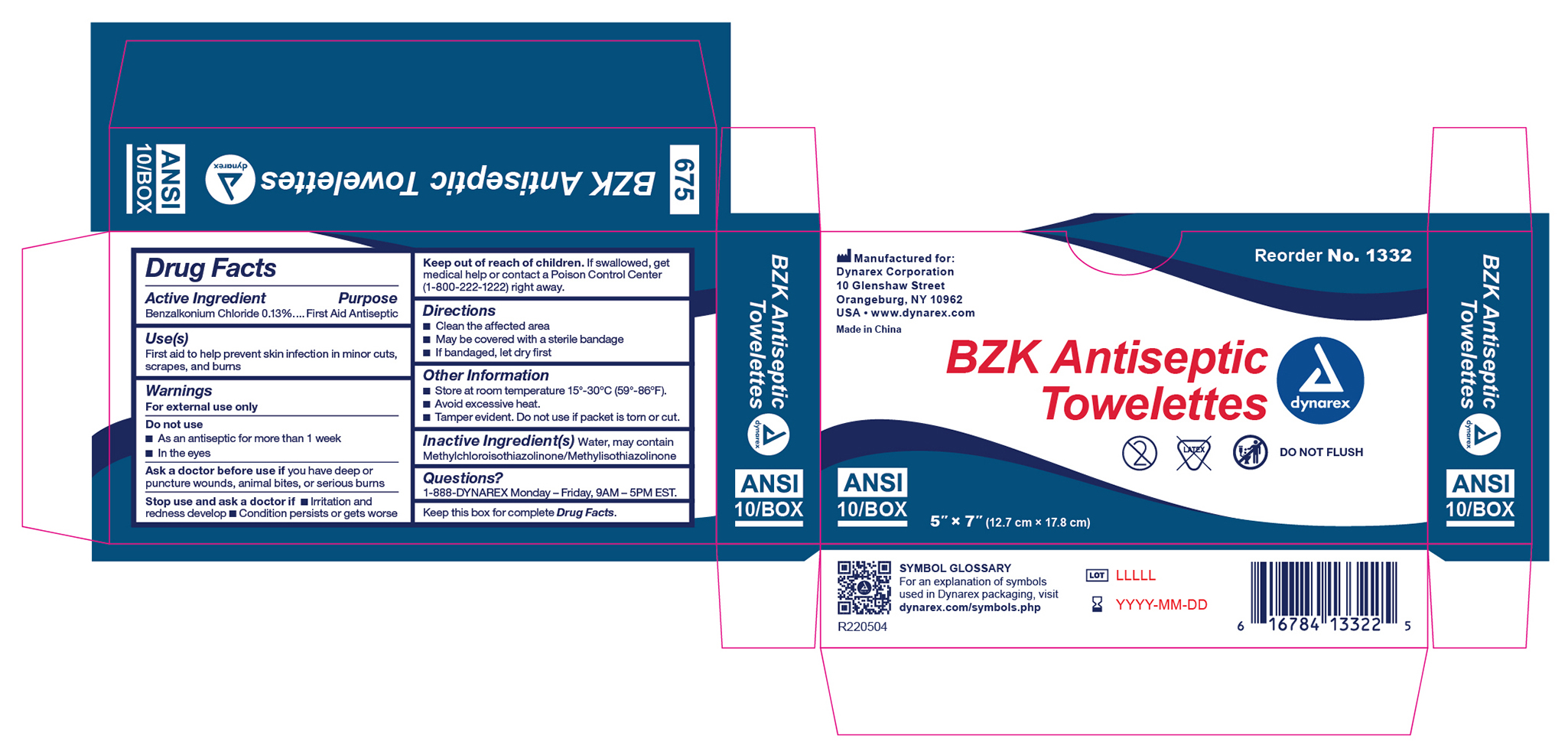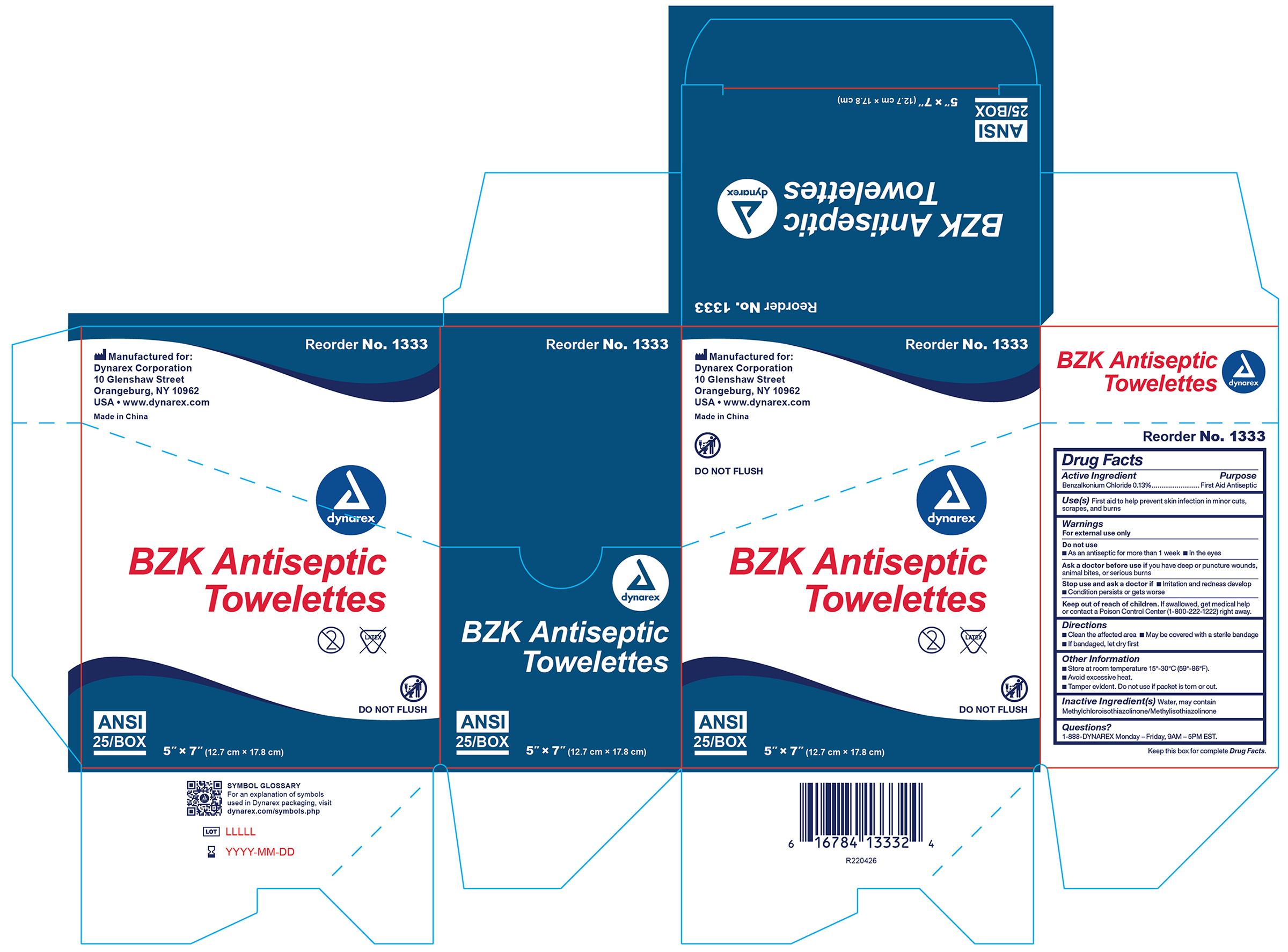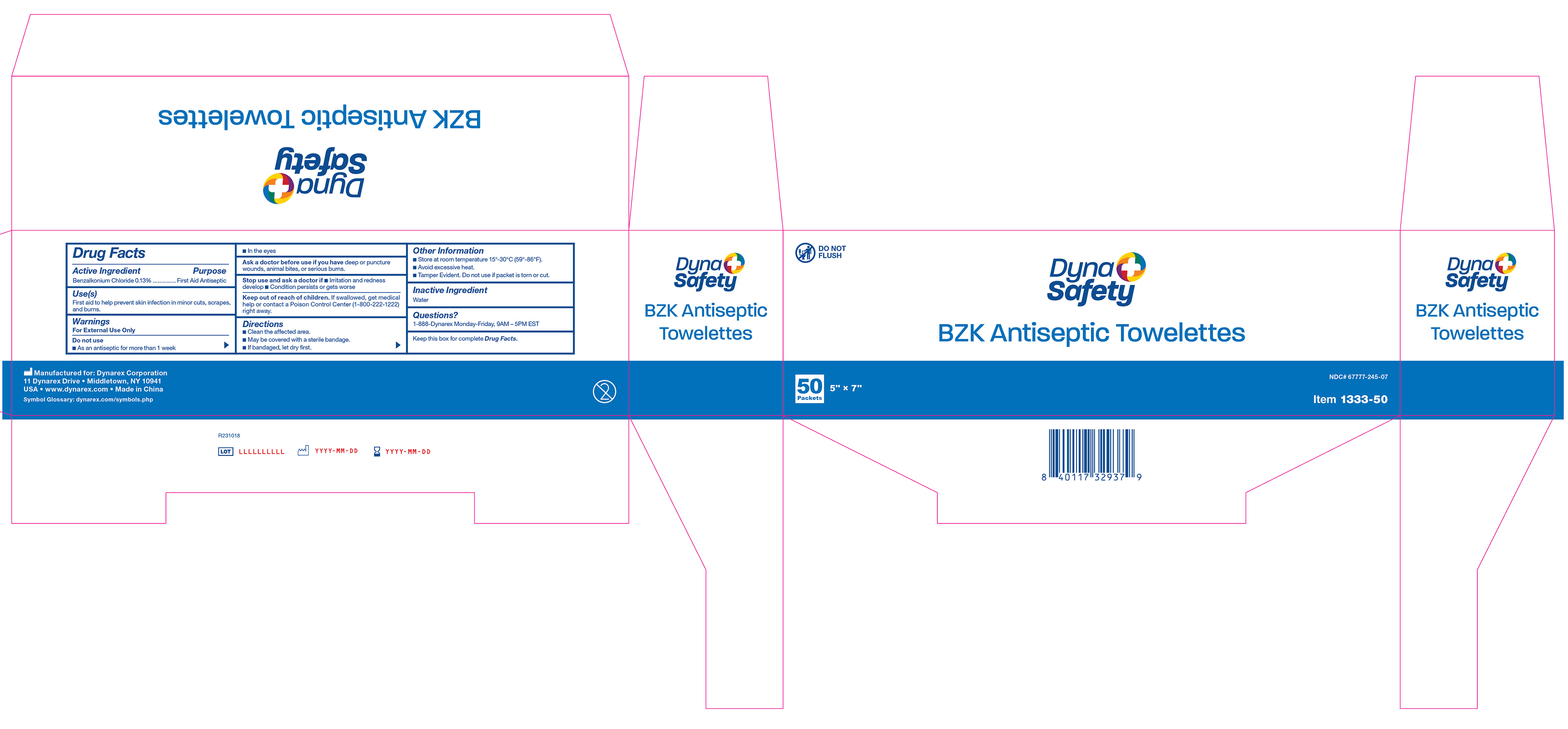 DRUG LABEL: BZK Pads
NDC: 67777-245 | Form: SWAB
Manufacturer: Dynarex Corporation
Category: otc | Type: HUMAN OTC DRUG LABEL
Date: 20260128

ACTIVE INGREDIENTS: BENZALKONIUM CHLORIDE 1.3 mg/1 mL
INACTIVE INGREDIENTS: WATER

1303 BZK Antiseptic Towelettes NDC 67777-245-01, 1331 BZK Antiseptic Towelettes NDC 67777-245-02
1332 BZK Antiseptic Towelettes NDC 67777-245-04, 1333 BZK Antiseptic Towelettes NDC 67777-245-05
1303UB-10 BZX Antiseptic Towelettes NDC 67777-245-16, 1303-40 BZK Antiseptic Towelettes NDC 67777-245-18
1333-50 BZK Antiseptic Towelettes NDC 67777-245-17

Active Ingredient

Benzalkonium Chloride 0.13%

Purpose

First Aid Antiseptic

Use(s)

First aid to help prevent skin infection in minor cuts, scrapes, and burns.

Warnings

For External Use Only

Do not use:

• As an antiseptic for more than 1 week

• In the eyes

Ask a doctor before use if you have

Deep or puncture wounds, animal bites, or serious burns.

Stop use and ask a doctor if

• Irritation and redness develop

• Condition persists or gets worse

Keep Out Of Reach Of Children.

If swallowed, get medical help or contact a Poison Control Center (1-800-222-1222) right away.

Directions

• Clean the affected area.

• May be covered with a sterile bandage.

• If bandaged, let dry first.

Other Information

• Store at room temperature 15º-30ºC (59º-86ºF).

• Avoid excessive heat.

• Tamper Evident. Do not use if packet is torn or cut.

Inactive ingredients

Water

Questions?

1-888-DYNAREX Monday - Friday, 9AM - 5PM EST

Label

1331

Label

1332

Label

1333

Label 1303UB-10

1303UB-10

Label 1303-40

1303-40

Label 1333-50

1333-50